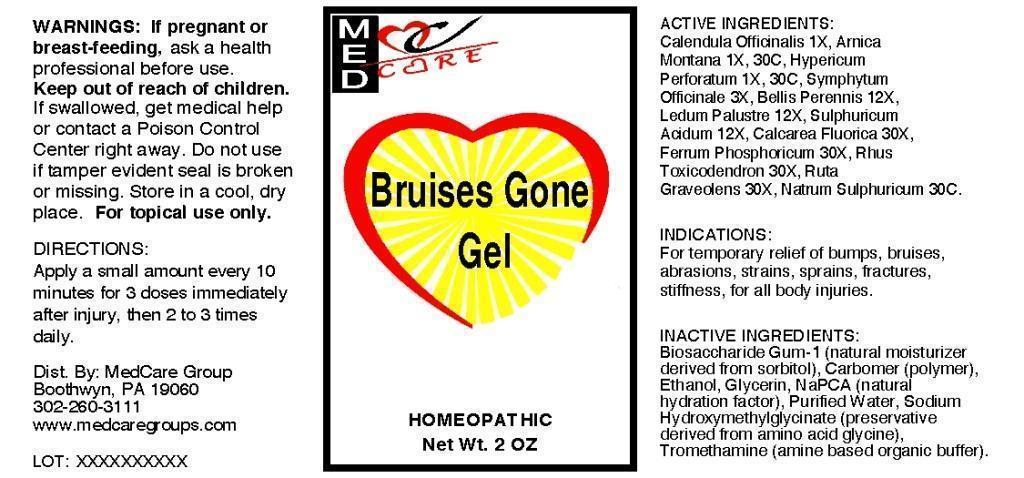 DRUG LABEL: Bruises Gone Gel
NDC: 54557-0002 | Form: GEL
Manufacturer: MedCare Group LLC
Category: homeopathic | Type: HUMAN OTC DRUG LABEL
Date: 20130808

ACTIVE INGREDIENTS: CALENDULA OFFICINALIS FLOWERING TOP 1 [hp_X]/1 mL; ARNICA MONTANA 1 [hp_X]/1 mL; HYPERICUM PERFORATUM 1 [hp_X]/1 mL; COMFREY ROOT 3 [hp_X]/1 mL; BELLIS PERENNIS 12 [hp_X]/1 mL; LEDUM PALUSTRE TWIG 12 [hp_X]/1 mL; SULFURIC ACID 12 [hp_X]/1 mL; CALCIUM FLUORIDE 30 [hp_X]/1 mL; FERRUM PHOSPHORICUM 30 [hp_X]/1 mL; TOXICODENDRON PUBESCENS LEAF 30 [hp_X]/1 mL; RUTA GRAVEOLENS FLOWERING TOP 30 [hp_X]/1 mL; SODIUM SULFATE 30 [hp_C]/1 mL
INACTIVE INGREDIENTS: BIOSACCHARIDE GUM-1; CARBOMER HOMOPOLYMER TYPE C; CETYL HYDROXYETHYLCELLULOSE (350000 MW); ALCOHOL; GLYCERIN; SODIUM PYRROLIDONE CARBOXYLATE; WATER; SODIUM HYDROXYMETHYLGLYCINATE; TROMETHAMINE

DRUG FACTS:

ACTIVE INGREDIENTS:

Calendula Officinalis 1X, Arnica Montana 1X, 30C, Hypericum Perforatum 1X, 30C, Symphytum Officinale 3X, Bellis perennis 12X, Ledum Palustre 12X, Sulphuricum Acidum 12X, Calcarea Fluorica 30X, Ferrum Phosphoricum 30X, Rhus Toxicodendron 30X, Ruta Graveolens 30X, Natrum Sulphuricum 30C.

INDICATIONS:

For temporary relief of bumps, bruises, abrasions, strains, sprains, fractures, stiffness, for all body injuries.

WARNINGS:

If pregnant or breast-feeding, ask a health professional before use.

Keep out of reach of children. If swallowed, get medical help or contact a Poison Control Center right away.

Do not use if tamper evident seal is broken or missing.

For topical use only.

STORAGE:

Store in a cool, dry place.

DIRECTIONS:

Apply a small amount every 10 minures for 3 doses immediately after injury, then 2 to 3 times daily.

INACTIVE INGREDIENTS:

Biosaccharide Gum-1, Carbomer, Ethanol, Glycerin, NaPCA, Purified Water, Sodium Hydroxymethylglycinate, Tromethamine.

Keep out of reach of children. If swallowed, get medical help or contact a Poison Control Center right away.

INDICATIONS:

For temporary relief of bumps, bruises, abrasions, strains, sprains, fractures, stiffness, for all body injuries.

QUESTIONS:

Dist. By: MedCare Group

Boothwyn, PA 19060

302-260-3111

www.medcaregroups.com

PACKAGE DISPLAY LABEL:

MedCare

Bruises Gone Gel

HOMEOPATHIC

Net Wt. 2 oz